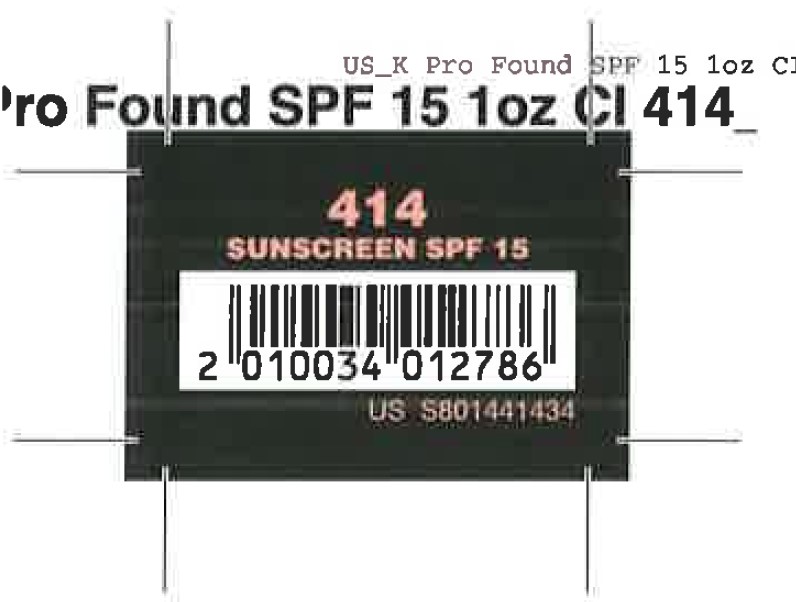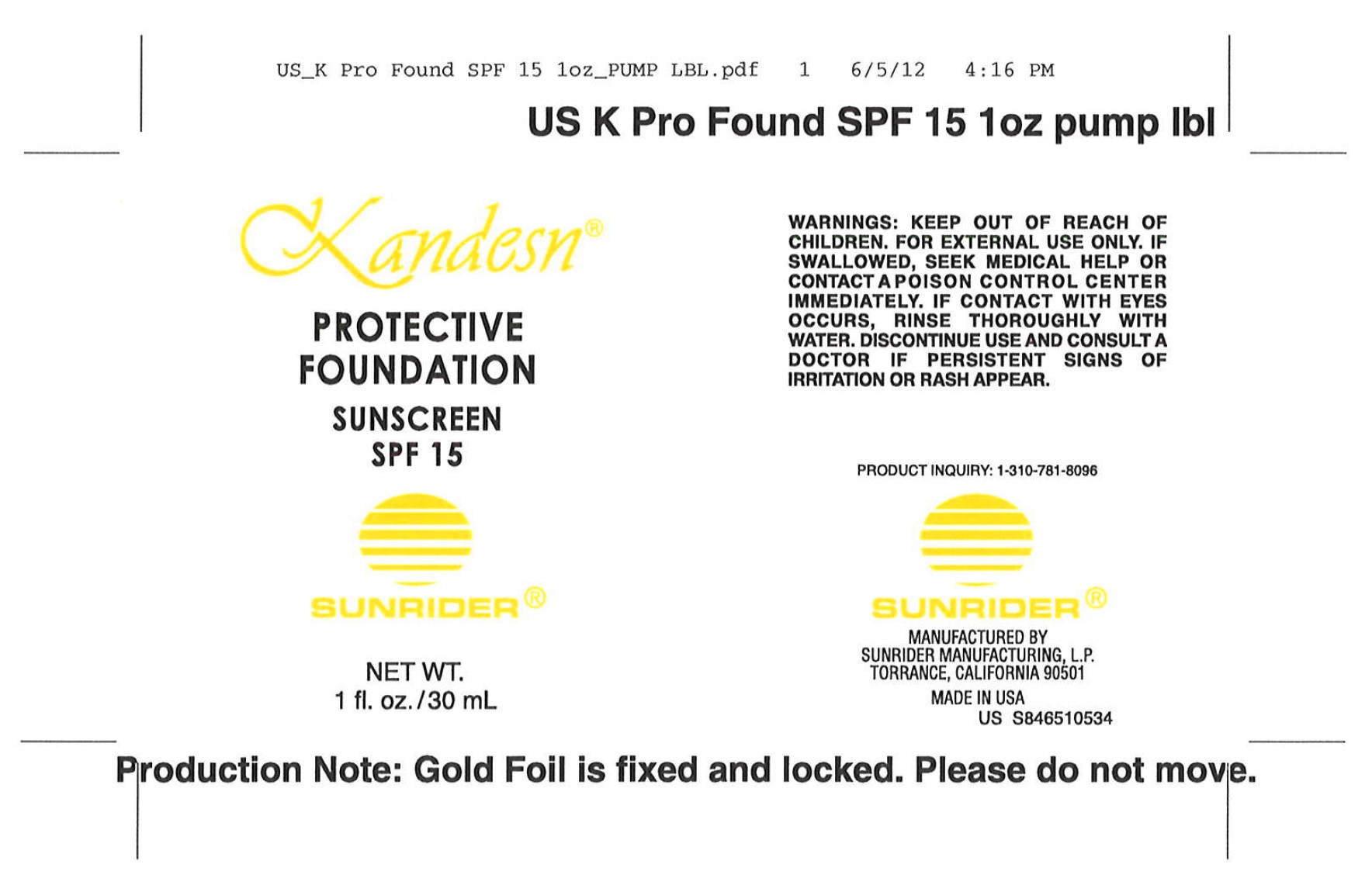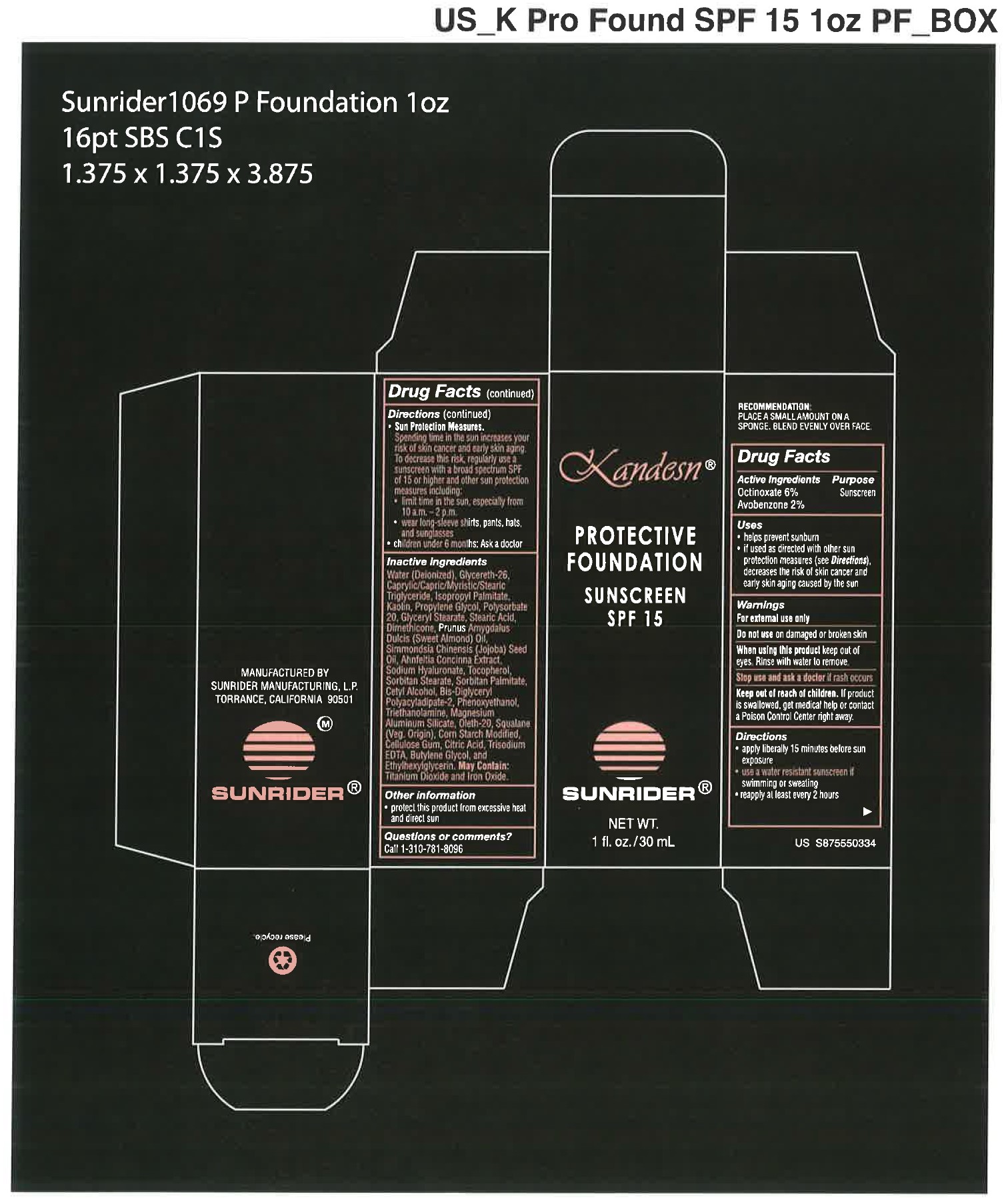 DRUG LABEL: Protective Foundation Sunscreen SPF 15
NDC: 62191-414 | Form: EMULSION
Manufacturer: Sunrider Manufacturing L.P.
Category: otc | Type: HUMAN OTC DRUG LABEL
Date: 20211208

ACTIVE INGREDIENTS: AVOBENZONE 0.02 g/1 g; OCTINOXATE 0.06 g/1 g
INACTIVE INGREDIENTS: water; ALMOND OIL; CARBOXYMETHYLCELLULOSE SODIUM; CETYL ALCOHOL; CITRIC ACID MONOHYDRATE; DIMETHICONE; EDETATE TRISODIUM; GLYCERETH-26; GLYCERYL MONOSTEARATE; HYALURONATE SODIUM; ISOPROPYL PALMITATE; KAOLIN; MAGNESIUM ALUMINUM SILICATE; OLETH-20; PHENOXYETHANOL; POLYSORBATE 20; PROPYLENE GLYCOL; SORBITAN MONOPALMITATE; SORBITAN MONOSTEARATE; SQUALENE; STEARIC ACID; TOCOPHEROL; TRICAPRIN; TRICAPRYLIN; TROLAMINE; AHNFELTIOPSIS CONCINNA; CAPRYLIC/CAPRIC/PALMITIC/STEARIC TRIGLYCERIDE; JOJOBA OIL; BIS-DIGLYCERYL POLYACYLADIPATE-2; CORN STARCH 3-E-DODECENYL SUCCINIC ANHYDRIDE MODIFIED; BUTYLENE GLYCOL; ETHYLHEXYLGLYCERIN

Protective Foundation Sunscreen SPF 15

USES:

- helps prevent sunburn
- if used as directed with other sun protection measures (see Directions), decreased the risk of skin cancer and early skin aging caused by the sun.

DOSAGE AND ADMINISTRATION

RECOMMENDATION: PLACE A SMALL AMOUNT ON A SPONGE, BLEND EVENLY OVER FACE

DIRECTIONS:

- apply liberally 15 minutes before sun exposure
- use a water resistant sunscreen if swimming or sweating
- reapply at least every 2 hours
- Sun Protection Measures. Spending time in the sun increases your risk of skin cancer and early skin againg. To decrease this risk, regularly use a sunscreen with a broad spectrum SPF of 15 or higher and other sun protection measures including:
  - limit time in the sun, expecially from 10 a.m. - 2 p.m.
  - wear long-sleeve shirts, pants, hats, and sunglasses
- Children under 6 months: Ask a doctor

ACTIVE INGREDIENTS:

OCTINOXATE 6%
AVOBENZONE 2%

INACTIVE INGREDIENT

OTHER INGREDIENTS:

Water (Deionized)
Glycereth-26
Caprylic/Capric/Myristic/Stearic Triglyceride
Isopropyl Palmitate
Kaolin
Propylene Glycol
Polysorbate 20
Glyceryl Stearate
Stearic Acid (Veg. Origin)
Dimethicone
Prunus Amygdalus Dulcis (Sweet Almond) Oil
Simmondsia Chinensis (Jojoba) Seed Oil
Ahnfeltia Concinna Extract
Sodium Hyaluronate
Tocopherol
Sorbitan Stearate
Sorbitan Palmitate
Cetyl Alcohol
Bis-Diglyceryl Polyacyladipate-2
Phenoxyethanol
Triethanolamine
Magnesium Aluminum Silicate
Oleth-20
Squalane (Veg. Origin)
Corn Starch Modified
Cellulose Gum
Citric Acid
Trisodium EDTA
Butylene Glycol
Ethylhexylglycerin

WARNINGS:

FOR EXTERNAL USE ONLY

Do not use on damaged or broken skin

When using this product keep oout of eyes. Rinse with water to remove.

Sto use and ask a doctor if rash occurs.

Keep out of reach of children. If product is swallowed, get medical help or contact a Poison Control Center right away.

KEEP OUT OF REACH OF CHILDREN. If product is swallowed, get medical help or contact a Poison Control Center right away.